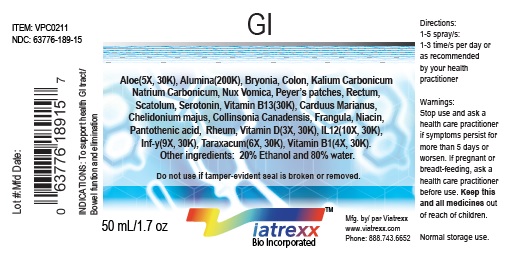 DRUG LABEL: Viatrexx-GI
NDC: 63776-189 | Form: SPRAY
Manufacturer: VIATREXX BIO INCORPORATED
Category: homeopathic | Type: HUMAN OTC DRUG LABEL
Date: 20190319

ACTIVE INGREDIENTS: Aloe 30 [kp_C]/1 mL; Aluminum Oxide 200 [kp_C]/1 mL; Bryonia Alba Root 30 [kp_C]/1 mL; Milk Thistle 200 [kp_C]/1 mL; Chelidonium Majus 30 [kp_C]/1 mL; Collinsonia Canadensis Root 30 [kp_C]/1 mL; Sus Scrofa Colon 30 [kp_C]/1 mL; Bos Taurus Colon 30 [kp_C]/1 mL; Frangula Alnus Bark 30 [kp_C]/1 mL; Interleukin-12 Human 30 [kp_C]/1 mL; Interferon Gamma-1a 30 [kp_C]/1 mL; Potassium Carbonate 30 [kp_C]/1 mL; Sodium Carbonate 30 [kp_C]/1 mL; Niacin 30 [kp_C]/1 mL; Strychnos Nux-Vomica Seed 30 [kp_C]/1 mL; Pantothenic Acid 30 [kp_C]/1 mL; Bos Taurus Peyer'S Patch 30 [kp_C]/1 mL; Sus Scrofa Peyer'S Patch 30 [kp_C]/1 mL; Sus Scrofa Rectum 30 [kp_C]/1 mL; Serotonin 30 [kp_C]/1 mL; Taraxacum Officinale 30 [kp_C]/1 mL; Thiamine 30 [kp_C]/1 mL; Vitamin D 30 [kp_C]/1 mL
INACTIVE INGREDIENTS: Alcohol; Water

GI

Active Ingredients

Aloe (5X, 30K), Alumina (200K), Byonia (30K), Carduus Marianus (3X, 30K), Chelidonium Majus (3X, 30K), Collinsonia Canadensis (3X, 30K), Colon (30K), Frangula (3X, 30K), IL 12 (10X, 30K), Inf-y (9X, 30K), Kalium Carbonicum (30K), Natrium Carbonicum (30K), Niacin (3X, 30K), Nux vomica (30K), Pantothenic Acid (3X, 30K), Peyer’s Patches (30K), Rectum (30K), Rheum (3X, 30K), Scatolum (30K), Serotonin (30K), Taraxacum (6X, 30K), Vitamin B1 (4X, 30K), Vitamin B13 (30K), Vitamin D (3X, 30K).

Purpose

Aloe
Alumina
Byonia
Carduus Marianus
Chelidonium Majus
Collinsonia Canadensis
Colon
Frangula
IL 12
Inf-y
Kalium Carbonicum
Natrium Carbonicum
Niacin
Nux vomica
Pantothenic Acid
Peyer’s Patches
Rectum
Rheum
Scatolum
Serotonin
Taraxacum
Vitamin B1
Vitamin B13
Vitamin D

Bowel function support
Constipation issues
Diarrhoea
Constipation
Liver bilary drainage
Hemorrhoids, constipation
Bowel function
Laxative
GI lining repair
GI lining repair
Hemorrhoids, intestinal catarrh
Diarrhoea
Lipid conversion, gut support
GI track balance, laxative
Metabolism
Immune support, Gut health
Hemorrhoids, peristaltic
Diarrhea, anal complaints
Leaky gut
Peristaltic movement
GI Drainage
GI health
GI health
GI health

Description

Viatrexx-GI is a homeopathic product composed of physiological (low dose and low low dose) natural micro nutrients. These nano particles are designed to nourish the system.

Uses

To support healthy GI tract/ Bowel function and elimination.

Warnings

Stop use and ask a health care practitioner if symptoms persist for more than five days or worsen. If pregnant or breastfeeding, ask a health care practitioner before use.

Dosage

1-3 spray(s); 1-3 time(s) per day or as recommended by your health care practitioner.

Inactive Ingredients

20% Alcohol and 80% Water

Other Information

Product availability

Product may be acquired in 0.5, 30, 50, 100, 250 mL bottles.

References upon request

To report SUSPECTED ADVERSE REACTIONS, contact the FDA at 1-800-FDA-1088 or www.fda.gov/medwatch

Distributed by
Viatrexx Bio Incorporated
Newark, DE, USA, 19713

Manufactured by
8046255 Canada Inc
Beloeil, Qc, J3G 6S3
Date of last revision March 2019

For Questions and comments
Info@Viatrexx.com
www.Viatrexx.com

PACKAGE LABEL.PRINCIPAL DISPLAY PANEL

NDC: 63776-189-11
Item: VPC0211
Viatrexx Bio Incorporated
Viatrexx-GI
Box of 1 X 0.5 mL ampule
For Oral and Topical Use
Expiry date: Lot #:
Manufactured for:
Viatrexx Bio Incorporated Newark, DE, USA, 19713
www.Viatrexx.com
Ingredients, homeopathic
See insert or www.viatrexx.com
Inactives: Alcohol 20%, Water 80%

NDC: 63776-189-14
Item: VPC0211
Viatrexx Bio Incorporated
Viatrexx-GI
Box of 1 X 30 mL spray bottle
For Oral and Topical Use
Expiry date: Lot #:
Manufactured for:
Viatrexx Bio Incorporated Newark, DE, USA, 19713
www.Viatrexx.com
Ingredients, homeopathic
See insert or www.viatrexx.com
Inactives: Alcohol 20%, Water 80%

NDC: 63776-189-15
Item: VPC0211
Viatrexx Bio Incorporated
Viatrexx-GI
Box of 1 X 50 mL spray bottle
For Oral and Topical Use
Expiry date: Lot #:
Manufactured for:
Viatrexx Bio Incorporated Newark, DE, USA, 19713
www.Viatrexx.com
Ingredients, homeopathic
See insert or www.viatrexx.com
Inactives: Alcohol 20%, Water 80%

NDC: 63776-189-16
Item: VPC0211
Viatrexx Bio Incorporated
Viatrexx-GI
Box of 1 X 100 mL bottle
For Oral and Topical Use
Expiry date: Lot #:
Manufactured for:
Viatrexx Bio Incorporated Newark, DE, USA, 19713
www.Viatrexx.com
Ingredients, homeopathic
See insert or www.viatrexx.com
Inactives: Alcohol 20%, Water 80%

NDC: 63776-189-17
Item: VPC0211
Viatrexx Bio Incorporated
Viatrexx-GI
Box of 1 X 250 mL bottle
For Oral and Topical Use
Expiry date: Lot #:
Manufactured for:
Viatrexx Bio Incorporated Newark, DE, USA, 19713
www.Viatrexx.com
Ingredients, homeopathic
See insert or www.viatrexx.com
Inactives: Alcohol 20%, Water 80%